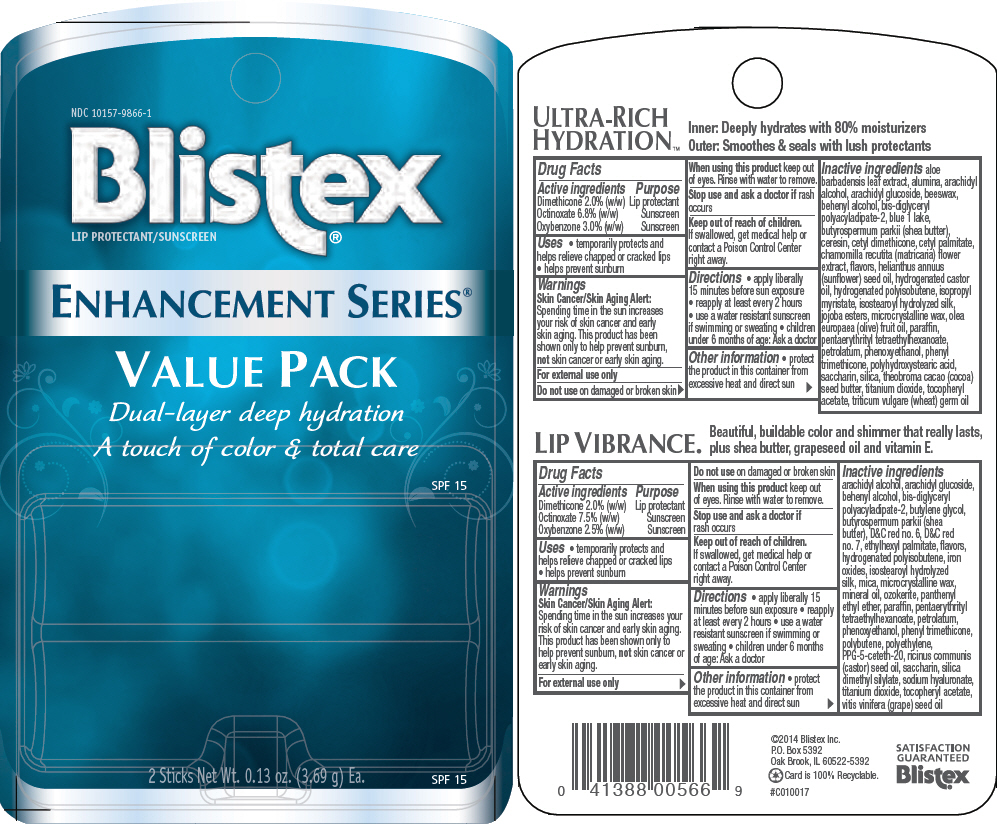 DRUG LABEL: Blistex Enhancement Series (Ultra-Rich Hydration and Lip Vibrance)
NDC: 10157-9866 | Form: KIT | Route: TOPICAL
Manufacturer: Blistex Inc.
Category: otc | Type: HUMAN OTC DRUG LABEL
Date: 20141204

ACTIVE INGREDIENTS: Dimethicone 2 g/100 g; Octinoxate 6.8 g/100 g; Oxybenzone 3 g/100 g; Dimethicone 2 g/100 g; Octinoxate 7.5 g/100 g; Oxybenzone 2.5 g/100 g
INACTIVE INGREDIENTS: yellow wax; pentaerythrityl tetraethylhexanoate; petrolatum; paraffin; hydrogenated castor oil; microcrystalline wax; isopropyl myristate; titanium dioxide; shea butter; aluminum oxide; silicon dioxide; cetyl palmitate; arachidyl alcohol; docosanol; arachidyl glucoside; olive oil; aloe vera leaf; .alpha.-tocopherol acetate; wheat germ oil; phenyl trimethicone; sunflower oil; chamomile; ceresin; cocoa butter; saccharin; FD&C blue no. 1; phenoxyethanol; arachidyl alcohol; ceresin; paraffin; microcrystalline wax; petrolatum; mineral oil; arachidyl glucoside; docosanol; butylene glycol; shea butter; D&C red no. 7; D&C red no. 6; ethylhexyl palmitate; phenoxyethanol; mica; panthenyl ethyl ether; pentaerythrityl tetraethylhexanoate; high density polyethylene; PPG-5-ceteth-20; ferric oxide red; titanium dioxide; phenyl trimethicone; grape seed oil; castor oil; sandalwood; saccharin; .alpha.-tocopherol acetate; silica dimethyl silylate; hyaluronate sodium; Polybutene (1400 MW)

Blistex® Enhancement Series® (Ultra-Rich Hydration™ and Lip Vibrance®)

ULTRA-RICH HYDRATION™

Drug Facts

ACTIVE INGREDIENT

Active ingredients | Purpose
Dimethicone 2.0% (w/w) | Lip protectant
Octinoxate 6.8% (w/w) | Sunscreen
Oxybenzone 3.0% (w/w) | Sunscreen

Uses

- temporarily protects and helps relieve chapped or cracked lips
- helps prevent sunburn

Warnings

Skin Cancer/Skin Aging Alert

Spending time in the sun increases your risk of skin cancer and early skin aging. This product has been shown only to help prevent sunburn, not skin cancer or early skin aging.

For external use only

Do not use on damaged or broken skin

When using this product keep out of eyes. Rinse with water to remove.

Stop use and ask a doctor if rash occurs

Keep out of reach of children. If swallowed, get medical help or contact a Poison Control Center right away.

Directions

- apply liberally 15 minutes before sun exposure
- reapply at least every 2 hours
- use a water resistant sunscreen if swimming or sweating
- children under 6 months of age: Ask a doctor

Other information

- protect the product in this container from excessive heat and direct sun

Inactive ingredients

aloe barbadensis leaf extract, alumina, arachidyl alcohol, arachidyl glucoside, beeswax, behenyl alcohol, bis-diglyceryl polyacyladipate-2, blue 1 lake, butyrospermum parkii (shea butter), ceresin, cetyl dimethicone, cetyl palmitate, chamomilla recutita (matricaria) flower extract, flavors, helianthus annuus (sunflower) seed oil, hydrogenated castor oil, hydrogenated polyisobutene, isopropyl myristate, isostearoyl hydrolyzed silk, jojoba esters, microcrystalline wax, olea europaea (olive) fruit oil, paraffin, pentaerythrityl tetraethylhexanoate, petrolatum, phenoxyethanol, phenyl trimethicone, polyhydroxystearic acid, saccharin, silica, theobroma cacao (cocoa) seed butter, titanium dioxide, tocopheryl acetate, triticum vulgare (wheat) germ oil

LIP VIBRANCE®

Drug Facts

ACTIVE INGREDIENT

Active ingredients | Purpose
Dimethicone 2.0% (w/w) | Lip protectant
Octinoxate 7.5% (w/w) | Sunscreen
Oxybenzone 2.5% (w/w) | Sunscreen

Uses

- temporarily protects and helps relieve chapped or cracked lips
- helps prevent sunburn

Warnings

Skin Cancer/Skin Aging Alert

Spending time in the sun increases your risk of skin cancer and early skin aging. This product has been shown only to help prevent sunburn, not skin cancer or early skin aging.

For external use only

Do not use on damaged or broken skin

When using this product keep out of eyes. Rinse with water to remove.

Stop use and ask a doctor if rash occurs

Keep out of reach of children. If swallowed, get medical help or contact a Poison Control Center right away.

Directions

- apply liberally 15 minutes before sun exposure
- reapply at least every 2 hours
- use a water resistant sunscreen if swimming or sweating
- children under 6 months of age: Ask a doctor

Other information

- protect the product in this container from excessive heat and direct sun

Inactive ingredients

arachidyl alcohol, arachidyl glucoside, behenyl alcohol, bis-diglyceryl polyacyladipate-2, butylene glycol, butyrospermum parkii (shea butter), D&C red no. 6, D&C red no. 7, ethylhexyl palmitate, flavors, hydrogenated polyisobutene, iron oxides, isostearoyl hydrolyzed silk, mica, microcrystalline wax, mineral oil, ozokerite, panthenyl ethyl ether, paraffin, pentaerythrityl tetraethylhexanoate, petrolatum, phenoxyethanol, phenyl trimethicone, polybutene, polyethylene, PPG-5-ceteth-20, ricinus communis (castor) seed oil, saccharin, silica dimethyl silylate, sodium hyaluronate, titanium dioxide, tocopheryl acetate, vitis vinifera (grape) seed oil

PRINCIPAL DISPLAY PANEL - Kit Blister Pack

NDC 10157-9866-1

Blistex®
LIP PROTECTANT/SUNSCREEN

ENHANCEMENT SERIES®

VALUE PACK

Dual-layer deep hydration

A touch of color & total care

SPF 15

2 Sticks Net Wt. 0.13 oz. (3.69 g) Ea.

SPF 15